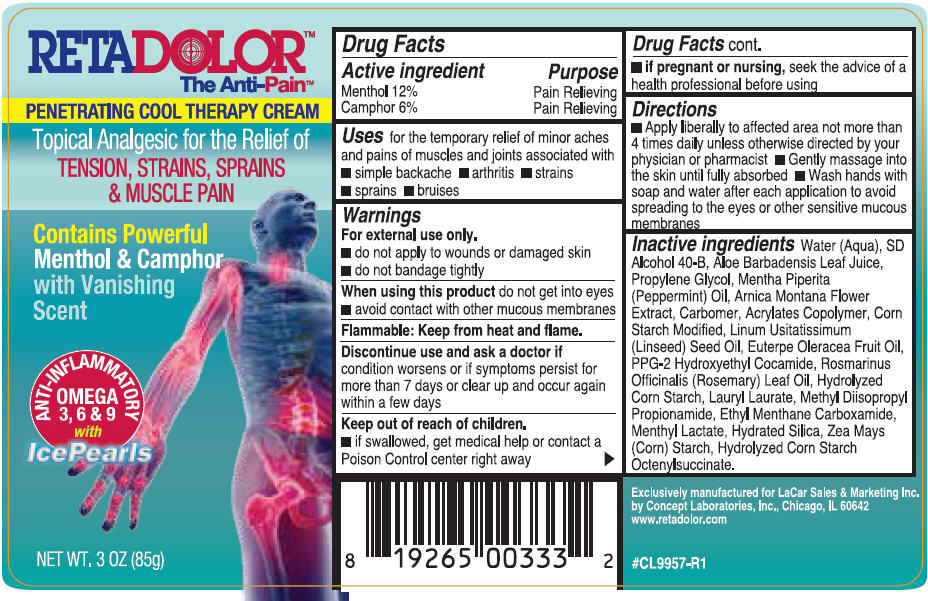 DRUG LABEL: Retadolor
NDC: 69279-241 | Form: CREAM
Manufacturer: LACAR SALES & MARKETING INC.
Category: otc | Type: HUMAN OTC DRUG LABEL
Date: 20170307

ACTIVE INGREDIENTS: MENTHOL, UNSPECIFIED FORM 0.12 g/1 g; CAMPHOR (SYNTHETIC) 0.06 g/1 g
INACTIVE INGREDIENTS: Water; ALOE VERA LEAF; PROPYLENE GLYCOL; PEPPERMINT OIL; ALCOHOL; STARCH, CORN; ARNICA MONTANA FLOWER; LINSEED OIL; ROSEMARY OIL; ACAI OIL; PPG-2 HYDROXYETHYL COCAMIDE; METHYL DIISOPROPYL PROPIONAMIDE; ETHYL MENTHANE CARBOXAMIDE; MENTHYL LACTATE, (-)-; LAURYL LAURATE; HYDRATED SILICA

Retadolor™
CREAM

Drug Facts

ACTIVE INGREDIENT

Active ingredient | Purpose
Menthol 12% | Pain Relieving
Camphor 6% | Pain Relieving

Uses

for the temporary relief of minor aches and pains of muscles and joints associated with

- simple backache
- arthritis
- strain
- sprains
- bruises

Warnings

For external use only.

- do not apply to wounds or damaged skin
- do not bandage tightly

When using this product do not get into eyes

- avoid contact with other mucous membranes

Flammable

Keep from heat and flame.

STOP USE

Discontinue use and ask a doctor if condition worsens or if symptoms persist for more than 7 days or clear up and occur again within a few days

Keep out of reach of children.

- if swallowed, get medical help or contact a Poison Control center right away
- if pregnant or nursing, seek the advice of a health professional before using

Directions

- Apply liberally to affected area not more than 4 times daily unless otherwise directed by your physician or pharmacist
- Gently massage into the skin until fully absorbed
- Wash hands with soap and water after each application to avoid spreading to the eyes or other sensitive mucous membranes

Inactive ingredients

Water (Aqua), SD Alcohol 40-B, Aloe Barbadensis Leaf Juice Propylene Glycol, Mentha Piperita (Peppermint) Oil, Arnica Montana Flower Extract, Carbomer, Acrylates Copolymer, Corn Starch Modified, Linum Usitatissimum (Linseed) Seed Oil, Euterpe Oleracea Fruit Oil, PPG-2 Hydroxyethyl Cocamide, Rosmarinus Officinalis (Rosemary) Leaf Oil, Hydrolyzed Corn Starch, Lauryl Laurate, Methyl Diisopropyl Propionamide, Ethyl Menthane Carboxamide, Menthyl Lactate, Hydrated Silica, Zea Mays (Corn) Starch, Hydrolyzed Corn Starch Octenylsuccinate.

PRINCIPAL DISPLAY PANEL - 85 g Bottle Label

RETADOLOR™
The Anti-Pain™

PENETRATING COOL THERAPY CREAM

Topical Analgesic for the Relief of
TENSION, STRAINS, SPRAINS
& MUSCLE PAIN

Contains Powerful
Menthol & Camphor
with Vanishing
Scent

ANTI-INFLAMMATORY
OMEGA
3, 6 & 9
with
IcePearls

NET WT. 3 OZ (85g)